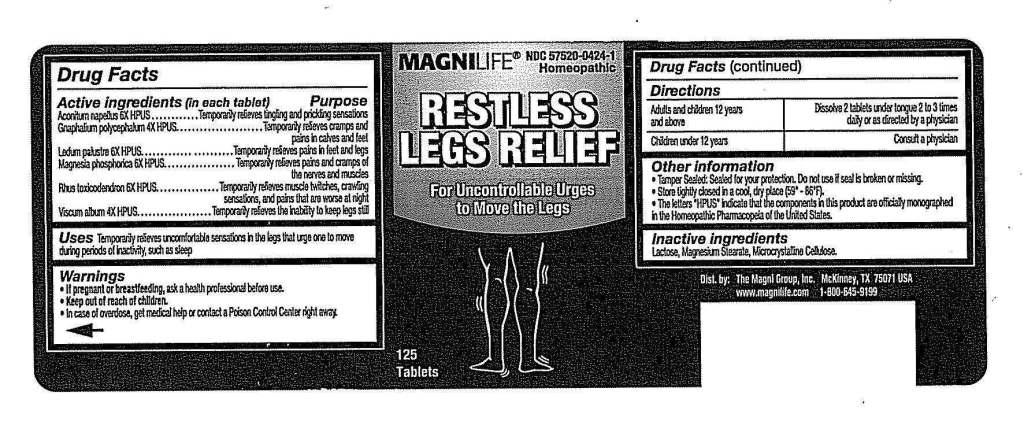 DRUG LABEL: Restless Legs Relief
NDC: 57520-0424 | Form: TABLET
Manufacturer: Apotheca Company
Category: homeopathic | Type: HUMAN OTC DRUG LABEL
Date: 20110516

ACTIVE INGREDIENTS: PSEUDOGNAPHALIUM OBTUSIFOLIUM 4 [hp_X]/1 1; VISCUM ALBUM FRUITING TOP     4 [hp_X]/1 1; ACONITUM NAPELLUS 6 [hp_X]/1 1; LEDUM PALUSTRE TWIG 6 [hp_X]/1 1; MAGNESIUM PHOSPHATE, DIBASIC TRIHYDRATE 6 [hp_X]/1 1; TOXICODENDRON PUBESCENS LEAF 6 [hp_X]/1 1
INACTIVE INGREDIENTS: CELLULOSE, MICROCRYSTALLINE; LACTOSE; MAGNESIUM STEARATE

Restless Legs Relief

ACTIVE INGREDIENT

ACTIVE INGREDIENTS: Gnaphalium polycephalum 4X, Viscum album 4X, Aconitum napellus 6X, Ledum palustre 6X, Magnesia phosphorica 6X, Rhus toxicodendron 6X.

PURPOSE

USES: Temporarily relieves uncomfortable sensations in the legs that urge one to move during periods of inactivity, such as sleep.

WARNINGS

WARNINGS: If pregnant or breastfeeding, ask a health professional before use.

Keep out of reach of children. In case of overdose, get medical help or contact a Poison Control Center right away.

OTHER INFORMATION: Tamper Sealed: Sealed for your protection. Do not use if seal is broken or missing.

Store tightly closed in a cool, dry place. (59-86 degrees f).

The letters "HPUS" indicate that the components in this product are officially monographed in the Homeopathic Pharmacopeia of the United States.

DOSAGE AND ADMINISTRATION

DIRECTIONS: Adults and children 12 years and above: Dissolve 2 tablets under tongue 2 to 3 times daily or as directed by a physician.

Children under 12 years: Consult a physician.

INACTIVE INGREDIENT

INACTIVE INGREDIENTS: Lactose, Magnesium stearate, Microcrystalline cellulose.

KEEP OUT OF REACH OF CHILDREN. In case of overdose, get medical help or contact a Poison Control Center right away.

INDICATIONS AND USAGE

USES: Temporarily relieves uncomfortable sensations in the legs that urge one to move during periods of inactivity, such as sleep.

QUESTIONS

Dist. by:

The Magni Group, Inc.

McKinney, TX 75070 USA

www.magnilife.com

1-800-645-9199

PACKAGE LABEL

MAGNILIFE

NDC 57520-0424-1

Homeopathic

RESTLESS LEGS RELIEF

For Uncontrollable Urges to Move the Legs

125 Tablets